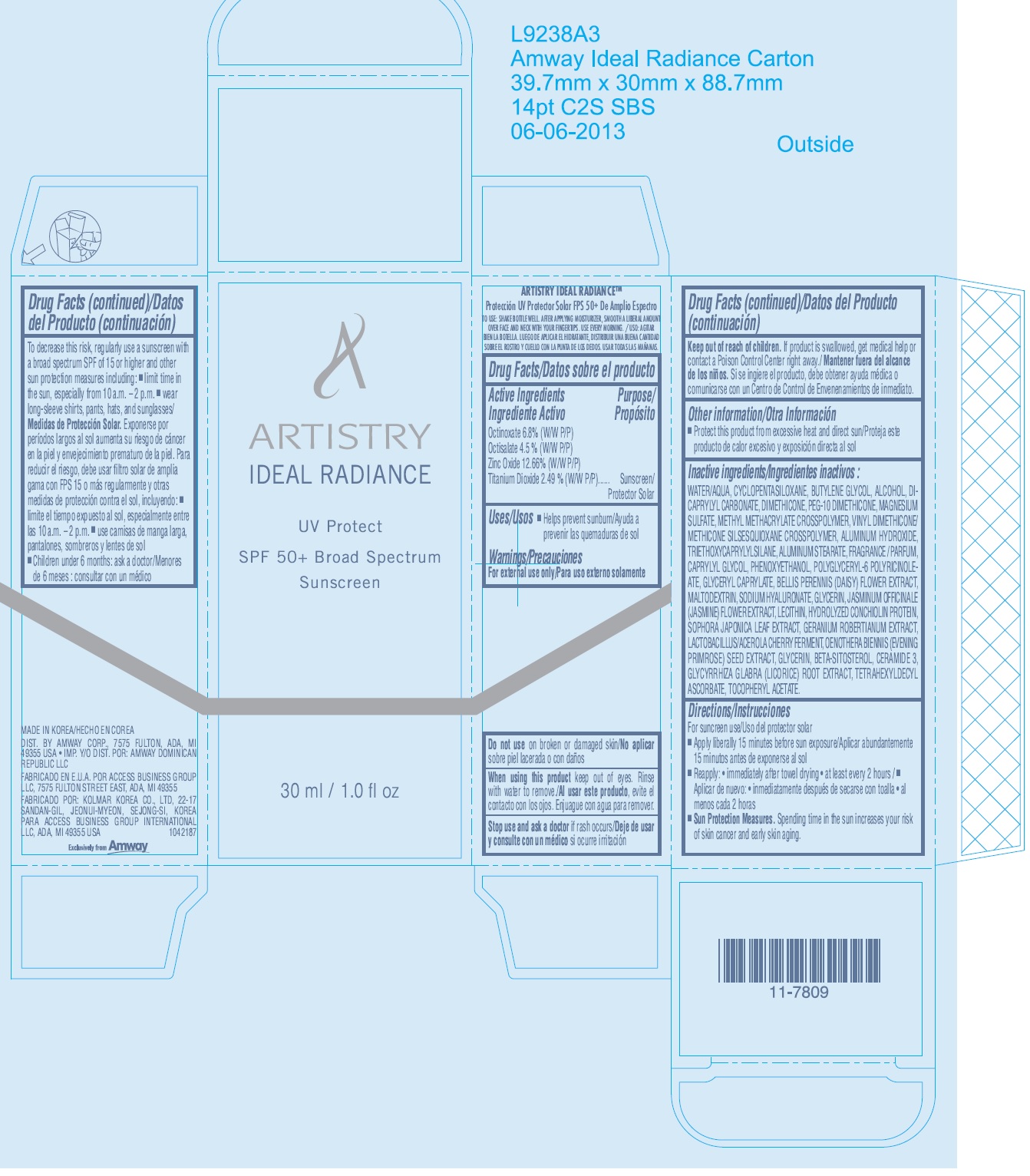 DRUG LABEL: ARTISTRY IDEAL RADIANCE UV Protect SPF 50 PLUS Broad Spectrum Sunscreen
NDC: 50390-108 | Form: CREAM
Manufacturer: Amway Corp
Category: otc | Type: HUMAN OTC DRUG LABEL
Date: 20240102

ACTIVE INGREDIENTS: OCTINOXATE 68 mg/1 mL; OCTISALATE 45 mg/1 mL; ZINC OXIDE 126.6 mg/1 mL; TITANIUM DIOXIDE 24.9 mg/1 mL
INACTIVE INGREDIENTS: WATER; CYCLOMETHICONE 5; BUTYLENE GLYCOL; ALCOHOL; DICAPRYLYL CARBONATE; DIMETHICONE; MAGNESIUM SULFATE, UNSPECIFIED FORM; METHYL METHACRYLATE; ALUMINUM HYDROXIDE; TRIETHOXYCAPRYLYLSILANE; ALUMINUM STEARATE; CAPRYLYL GLYCOL; PHENOXYETHANOL; GLYCERYL CAPRYLATE; BELLIS PERENNIS; MALTODEXTRIN; HYALURONATE SODIUM; GLYCERIN; JASMINUM OFFICINALE FLOWER; STYPHNOLOBIUM JAPONICUM LEAF; GERANIUM ROBERTIANUM; ACEROLA; OENOTHERA BIENNIS SEED; .BETA.-SITOSTEROL; CERAMIDE 3; GLYCYRRHIZA GLABRA; TETRAHEXYLDECYL ASCORBATE; .ALPHA.-TOCOPHEROL ACETATE

ARTISTRY IDEAL RADIANCE UV Protect SPF 50+ Broad Spectrum Sunscreen

Active Ingredients

Octinoxate 6.8% (W/W P/P) Octisalate 4.5% (W/W P/P) Zinc Oxide 12.66% (W/W P/P) Titanium Dioxide 2.49% (W/W P/P)

Purpose

Sunscreen

Uses

Helps prevent sunburn

Warnings

For external use only

Do not use

on broken or damaged skin

When using this product

keep out of eyes. Rinse with water to remove.

Stop use and ask a doctor

if rash occurs

Keep out of reach of children.

If product is swallowed, get medical help or contact a Poison Control Center right away.

Other information

Protect this product from excessive heat and direct sun

Inactive ingredients

WATER/AQUA, CYCLOPENTASILOXANE, BUTYLENE GLYCOL, ALCOHOL, DICAPRYLYL CARBONATE, DIMETHICONE, PEG-10 DIMETHICONE, MAGNESIUM SULFATE, METHYL METHACRYLATE CROSSPOLYMER, VINYL DIMETHICONE/ METHICONE SILSESQUIOXANE CROSSPOLYMER, ALUMINUM HYDROXIDE, TRIETHOXYCAPRYLYLSILANE, ALUMINUM STEARATE, FRAGRANCE / PARFUM, CAPRYLYL GLYCOL, PHENOXYETHANOL, POLYGLYCERYL-6 POLYRICINOLEATE, GLYCERYL CAPRYLATE, BELLIS PERENNIS (DAISY) FLOWER EXTRACT, MALTODEXTRIN, SODIUM HYALURONATE, GLYCERIN, JASMINUM OFFICINALE(JASMINE) FLOWER EXTRACT, LECITHIN, HYDROLYZED CONCHIOLIN PROTEIN, SOPHORA JAPONICA LEAF EXTRACT, GERANIUM ROBERTIANUM EXTRACT, LACTOBACILLUS/ACEROLA CHERRY FERMENT, OENOTHERA BIENNIS (EVENING PRIMROSE) SEED EXTRACT, GLYCERIN, BETA-SITOSTEROL, CERAMIDE 3, GLYCYRRHIZA GLABRA (LICORICE) ROOT EXTRACT, TETRAHEXYLDECYL ASCORBATE, TOCOPHERYL ACETATE.

Directions

For sunscreen use

To decrease this risk, regularly use a sunscreen with a broad spectrum SPF of 15 or higher and other sun protection measures including:

- Apply liberally 15 minutes before sun exposure
- Reapply: immediately after towel drying, at least every 2 hours
- Sun Protection Measures: Spending time in the sun increases your risk of skin cancer and early skin aging.

- limit time in the sun, especially from 10 a.m. – 2 p.m.
- wear long-sleeve shirts, pants, hats, and sunglasses